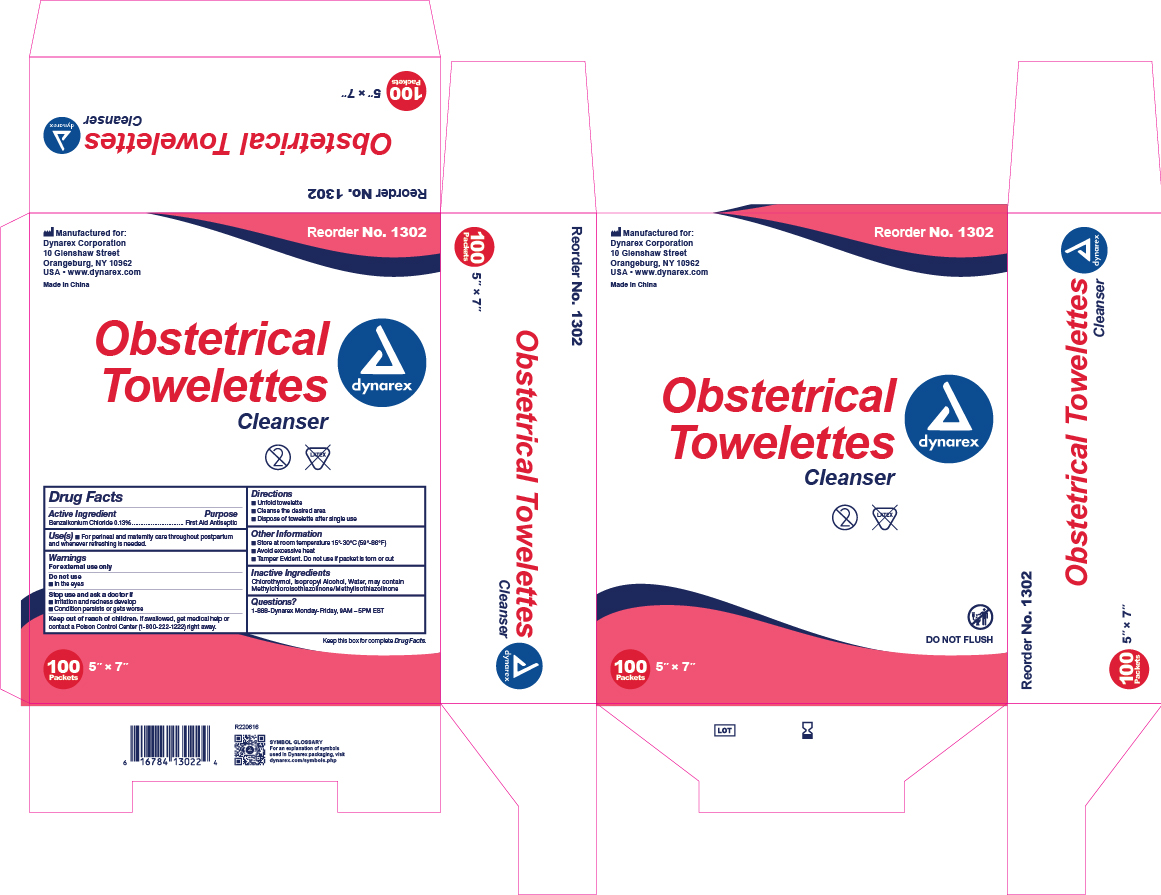 DRUG LABEL: BZK Pads
NDC: 67777-244 | Form: SWAB
Manufacturer: Dynarex Corporation
Category: otc | Type: HUMAN OTC DRUG LABEL
Date: 20260123

ACTIVE INGREDIENTS: BENZALKONIUM CHLORIDE 1.3 mg/1 mL
INACTIVE INGREDIENTS: CHLOROTHYMOL; ISOPROPYL ALCOHOL; WATER; METHYLCHLOROISOTHIAZOLINONE/METHYLISOTHIAZOLINONE MIXTURE

1302 Cleansing Towelettes NDC 67777-244-01

Active Ingredient

Benzalkonium Chloride 0.13% v/v

Purpose

First Aid Antiseptic

Uses

• For perineal and maternity care throughout postpartum and whenever refreshing is needed.

Warnings

For external use only

Do not use

• In the eye

Stop use and ask a doctor if

• Irritation and redness develop

• If condition persists for gets worse

Keep out of reach of children

If swallowed, get medical help or contact a Poison Control Center (1-800-222-1222) right away.

Directions

• Unfold towel

• Cleanse the desired area

• Dispose of towlette after single use.

Other Information

• Store at room temperature 15º-30ºC (59º-86ºF)

• Avoid excessive heat.

• Tamper evident. Do not use if packet is torn or cut.

Inactive ingredients

Chlorothymol, Isopropyl Acohol, Water, may contain Methylchloroisothiazolinone/Methylisothiazolinone

Label

1302 Label